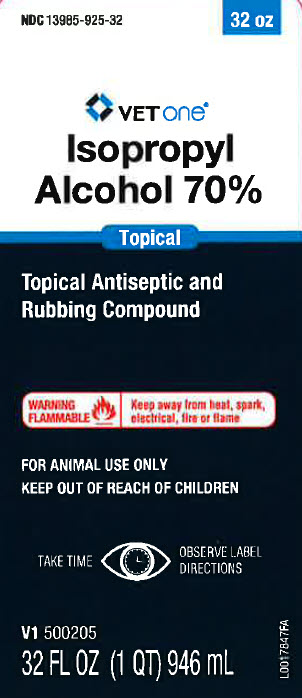 DRUG LABEL: Isopropyl Alcohol
NDC: 13985-925 | Form: SOLUTION
Manufacturer: MWI/VETONE
Category: animal | Type: OTC ANIMAL DRUG LABEL
Date: 20250317

ACTIVE INGREDIENTS: ISOPROPYL ALCOHOL 70 mL/100 mL
INACTIVE INGREDIENTS: WATER

Vetone 535.000/535AA /810
70% Isopropyl Alcohol for Animal Care

Ingredients

ACTIVE INGREDIENT: Isopropyl alcohol 70%

INACTIVE INGREDIENT: Water

Indications and Use

INDICATIONS: For external use only as an antiseptic and rubelacient.

DIRECTIONS FOR USE: Use full strength as a topical antiseptic. May be used for temporary relief of minor muscular aches or pain due to overexertion and fatigue. Apply full strength to affected area and massage briskly to stimulate circulation.

PRECAUTIONS

FOR EXTERNAL USE ONLY

CAUTION: In case of deep or puncture wounds or serious burns, consult a veterinarian. If redness, irritation, or swelling persists or increases, discontinue use and consult a veterinarian. Do not apply to irritated skin or if excessive irritation develops.

Warnings

WARNING: If taken internally, serious gastric disturbance will result. Avoid contact with eyes or mucous membranes.

WARNING! FLAMMABLE! KEEP AWAY FROM HEAT AND OPEN FLAME!

First Aid: If swallowed, induce vomiting or use stomach pump. In case of eye contact, flush thoroughly with water. Seek medical attention.

Storage

Store at a temperature between 15º-30ºC (59º-86ºF). Keep container tightly closed when not in use.

Adverse event

Distributed by: MWI, Boise, ID 83705

www.VetOne.net

Principal Panel Display

NDC 13985-925-32

VetOne

Isopropyl Alcohol 70%

Topical Antiseptic and Rubbing Compound

WARNING FLAMMABLE. Keep away from heat, spark, electrical, fire or flame.

FOR ANIMAL USE ONLY

KEEP OUT OF REACH OF CHILDREN

Take time. Observe label directions

32 FL OZ (1 QT) 946 mL